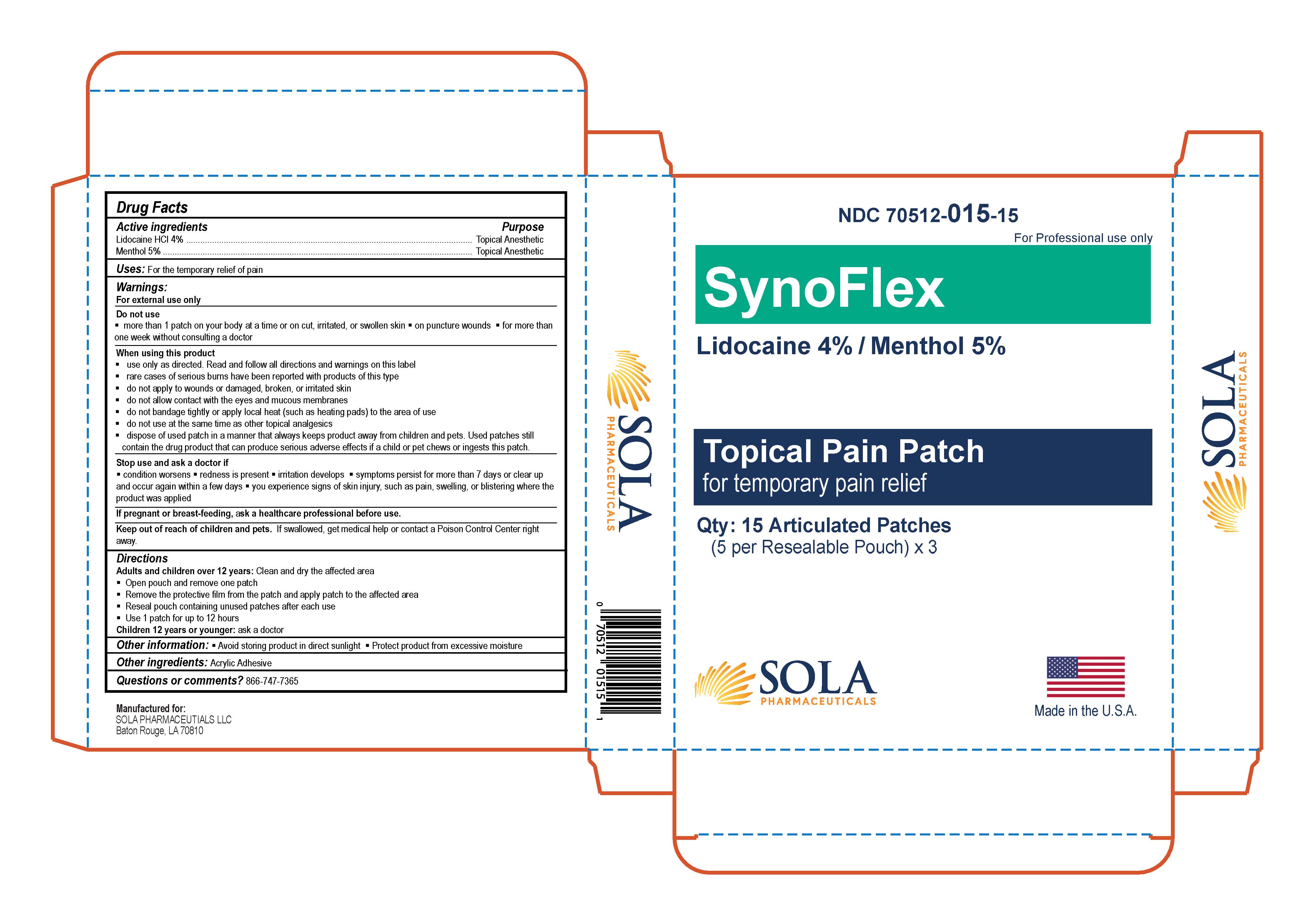 DRUG LABEL: SynoFlex Patch
NDC: 70512-015 | Form: PATCH
Manufacturer: Sola Pharmaceuticals
Category: otc | Type: HUMAN OTC DRUG LABEL
Date: 20251208

ACTIVE INGREDIENTS: LIDOCAINE HYDROCHLORIDE 40 mg/1 g; MENTHOL 50 mg/1 g
INACTIVE INGREDIENTS: ACRYLIC ACID

SynoFlex Patch

Active Ingredients

Lidocaine Hcl 4%

Menthol 5%

Purpose

Topical Anesthetic

Uses

For the temporary relief of pain

Warnings

For external use only

Do not use

- More than 1 patch on your body at a time or on cut, irritated, or swollen skin
- On puncture wounds
- For more than one week without consulting a doctor

When using this product

- use only as directed. Read and follow all directions and warnings on this label
- rare cases of serious burns have been reported with products of this type
- do not apply to wounds or damaged, broken, or irritated skin
- do not allow contact with the eyes and mucous membranes
- do not bandage tightly or apply local heat (such as heating pads) to the area of use
- do not use at the same time as other topical analgesics
- dispose of used patch in a manner that always keeps product away from children and pets. Used patches still contain the drug product that can produce serious adverse effects if a child or pet chews or ingests this patch.

Stop use and ask a doctor if

- condition worsens
- redness is present
- irritation develops
- symptoms persist for more than 7 days or clear up and occur again within a few days
- you experience signs of skin injury, such as pain, swelling, or blistering where the product was applied

If pregnant or breast-feeding

ask a healthcare professional before use.

Keep out of reach of children and pets

If swallowed, get medical help or contact a Poison Control Center right away.

Directions

Adults and children over 12 years: Clean and dry the affected area

- Open pouch and remove one patch
- Remove the protective film from the patch and apply patch to the affected area
- Reseal pouch containing unused patches after each use
- Use 1 patch for up to 12 hours

Children 12 years or younger: ask a doctor

Other Information

- Avoid storing product in direct sunlight
- Protect product from excessive moisture

Other Ingredients

Acrylic Adhesive

Questrions or comments?

866-747-7365

PACKAGE LABEL

Manufactured for:

Sola Pharmaceuticals LLC

Baton Rouge, LA 70810

SynoFlex Patch

Topical Pain Patch

For temporary relief of pain

NDC 70512-015-15

Qty: 15 Flex Patches

(5 per Resealable Pouch) x 3